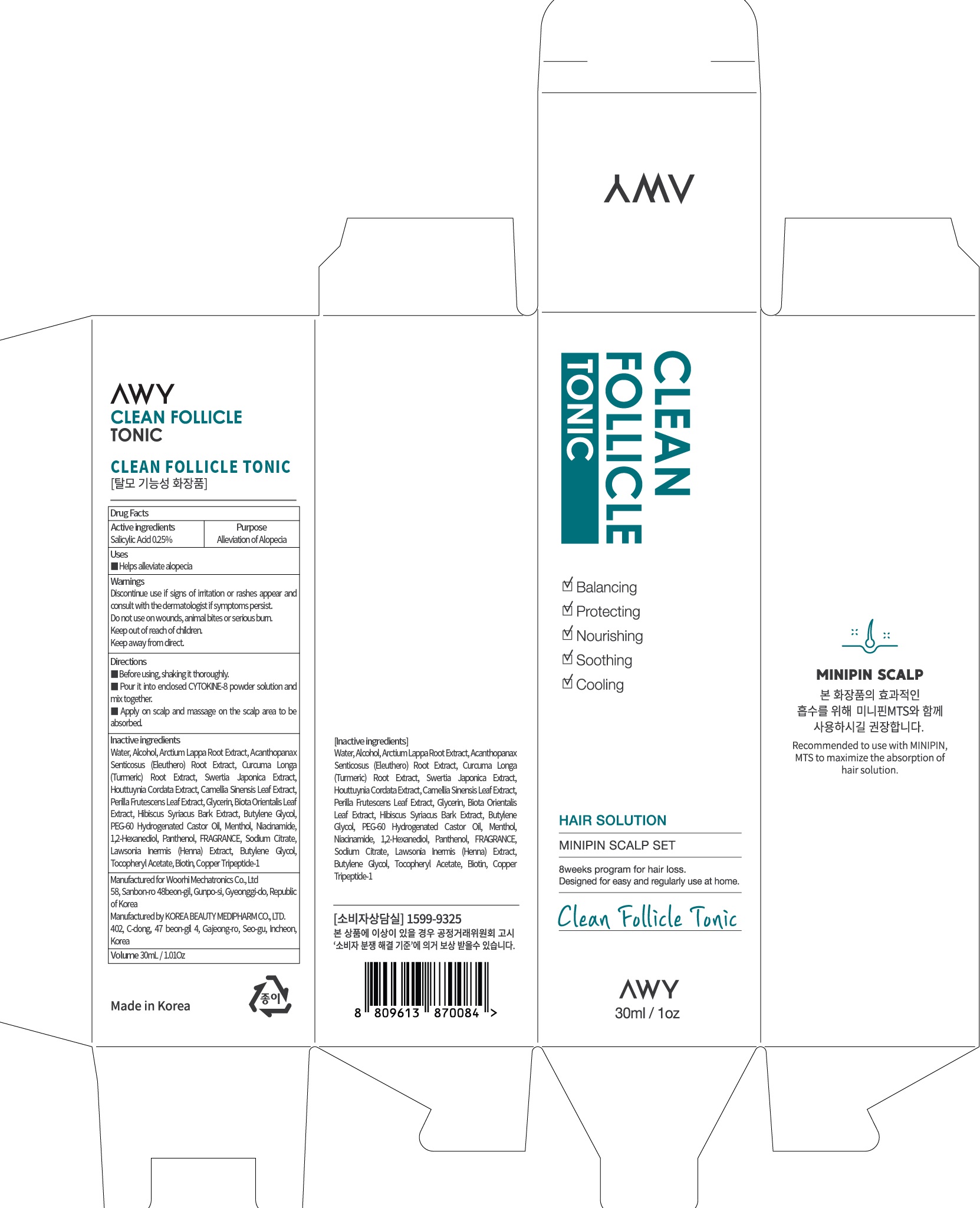 DRUG LABEL: CLEAN FOLLICLE TONIC
NDC: 72729-050 | Form: LIQUID
Manufacturer: Woorhi Mechatronics Co., Ltd.
Category: otc | Type: HUMAN OTC DRUG LABEL
Date: 20210209

ACTIVE INGREDIENTS: Salicylic Acid 0.07 g/30 mL
INACTIVE INGREDIENTS: Water; Alcohol

ACTIVE INGREDIENT

Salicylic Acid 0.25%

INACTIVE INGREDIENTS

Water, Alcohol, Arctium Lappa Root Extract, Acanthopanax Senticosus (Eleuthero) Root Extract, Curcuma Longa (Turmeric) Root Extract, Swertia Japonica Extract, Houttuynia Cordata Extract, Camellia Sinensis Leaf Extract, Perilla Frutescens Leaf Extract, Glycerin, Biota Orientalis Leaf Extract, Hibiscus Syriacus Bark Extract, Butylene Glycol, PEG-60 Hydrogenated Castor Oil, Menthol, Niacinamide, 1,2-Hexanediol, Panthenol, FRAGRANCE, Sodium Citrate, Lawsonia Inermis (Henna) Extract, Butylene Glycol, Tocopheryl Acetate, Biotin, Copper Tripeptide-1

PURPOSE

Alleviation of Alopecia

WARNINGS

Discontinue use if signs of irritation or rashes appear and consult with the dermatologist if symptoms persist.

Do not use on wounds, animal bites or serious burn.

Keep out of reach of children.

Keep away from direct.

KEEP OUT OF REACH OF CHILDREN

Uses

Helps alleviate alopecia

Directions

■ Before using, shaking it thoroughly.

■ Pour it into enclosed CYTOKINE-8 powder solution and mix together.

■ Apply on scalp and massage on the scalp area to be absorbed.